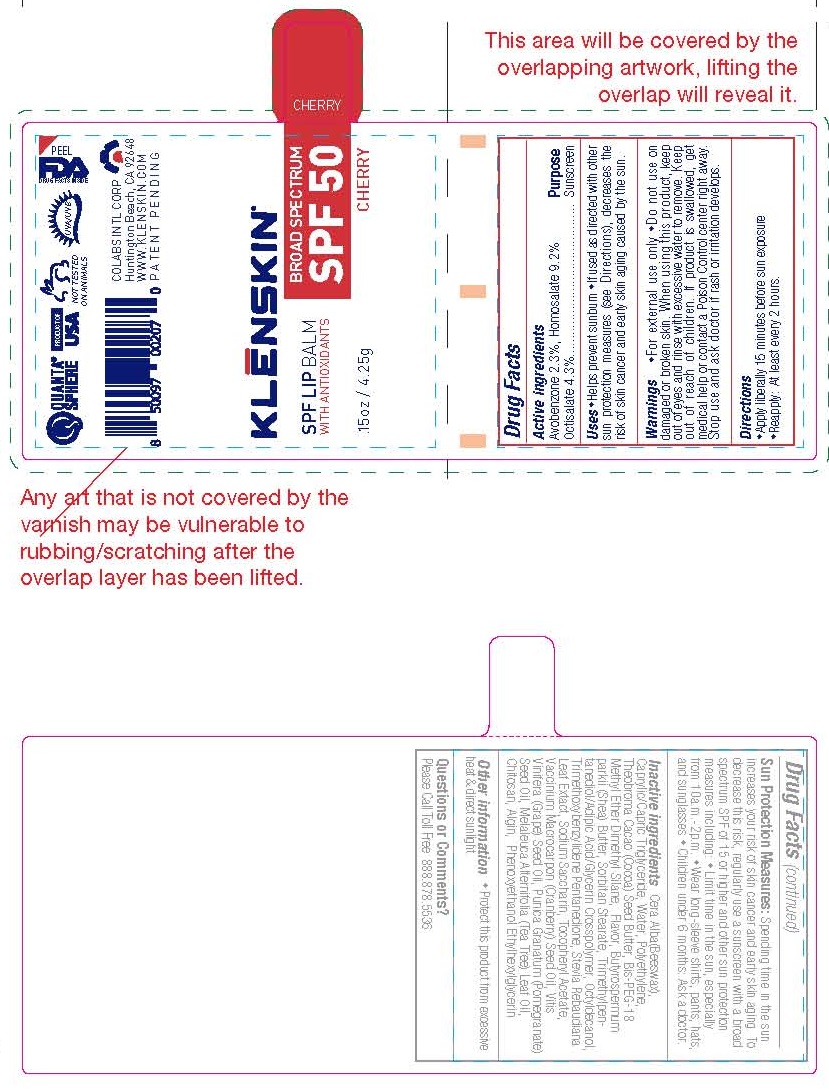 DRUG LABEL: KLENSKIN SPF LIP BALM BROAD SPECTRUM
NDC: 61369-301 | Form: LIPSTICK
Manufacturer: CoLabs Intl. Corp
Category: otc | Type: HUMAN OTC DRUG LABEL
Date: 20240115

ACTIVE INGREDIENTS: AVOBENZONE 2.3 g/100 g; HOMOSALATE 9.2 g/100 g; OCTISALATE 4.3 g/100 g
INACTIVE INGREDIENTS: YELLOW WAX; MEDIUM-CHAIN TRIGLYCERIDES; WATER; HIGH DENSITY POLYETHYLENE; COCOA BUTTER; BIS-PEG-18 METHYL ETHER DIMETHYL SILANE; SHEA BUTTER; SORBITAN MONOSTEARATE; TRIMETHYLPENTANEDIOL/ADIPIC ACID/GLYCERIN CROSSPOLYMER (25000 MPA.S); OCTYLDODECANOL; TRIMETHOXYBENZYLIDENE PENTANEDIONE; STEVIA REBAUDIUNA LEAF; SACCHARIN SODIUM; .ALPHA.-TOCOPHEROL ACETATE; CRANBERRY SEED OIL; GRAPE SEED OIL; POMEGRANATE SEED OIL; TEA TREE OIL; CHITOSAN HIGH MOLECULAR WEIGHT (400-800 MPA.S); SODIUM ALGINATE; PHENOXYETHANOL; ETHYLHEXYLGLYCERIN

COLABS - KLENSKIN SPF LIP BALM BROAD SPECTRUM (61369-301)

ACTIVE INGREDIENTS

Avobenzone 2.3%

Homosalate 9.2%

Octisalate 4.3%

PURPOSE

SUNSCREEN

USES

- Helps prevent sunburn
- If used as directed with othersun protection measures (see Directions), decreases therisk of skin cancer and early skin aging caused by the sun.

WARNINGS

- For external use only
- Do not use ondamaged or broken skin. When using this product, keepout of eyes and rinse with excessive water to remove.

KEEP OUT OF REACH OF CHILDREN. IF PRODUCT IS SWALLOWED, GET MEDICAL HELP OR CONTACT A POISON CONTROL CENTER RIGHT AWAY.

STOP USE AND ASK A DOCTOR IF RASH OR IRRITATION DEVELOPS.

DIRECTIONS

Apply liberally 15 minutes before sun exposure

- Reapply: • At least every 2 hours

OTHER INFORMATION

Spending time in the sun increases your risk of skin cancer and early skin aging. To decrease this risk, regularly use a sunscreen with a broad spectrum SPF of 15 or higher and other sun protection measures including: • Limit time in the sun, especially from 10a.m.-2p.m. • Wear long-sleeve shirts, pants, hats, and sunglasses • Children under 6 months: Ask a doctor.

• Protect this product from excessive heat & direct sunlight.

INACTIVE INGREDIENTS

Cera Alba (Beeswax), Caprylic/Capric Triglyceride, Water, Polyethylene, Theobroma Cacao (Cocoa) Seed Butter, Bis-PEG-18 Methyl Ether Dimethyl Silane, Flavor, Butyrospermum parkii (Shea) Butter, Sorbitan Stearate, Trimethylpentanediol/Adipic Acid/Glycerin Crosspolymer, Octyldecanol, Trimethoxybenzylidene Pentanedione, Stevia Rebaudiana Leaf Extact, Sodium Saccharin, Tocopheryl Acetate, Vaccinium Macrocarpon (Cranberry) Seed Oil, Vitis Vinifera (Grape) Seed Oil, Punica Granatum (Pomegranate) Seed Oil, Melaleuca Alternifolia (Tea Tree) Leaf Oil, Chitosan, Algin, Phenoxyethanol, Ethylhexylglycerin

QUESTIONS OR COMMENTS?

PLEASE CALL TOLL FREE 888.878.5536